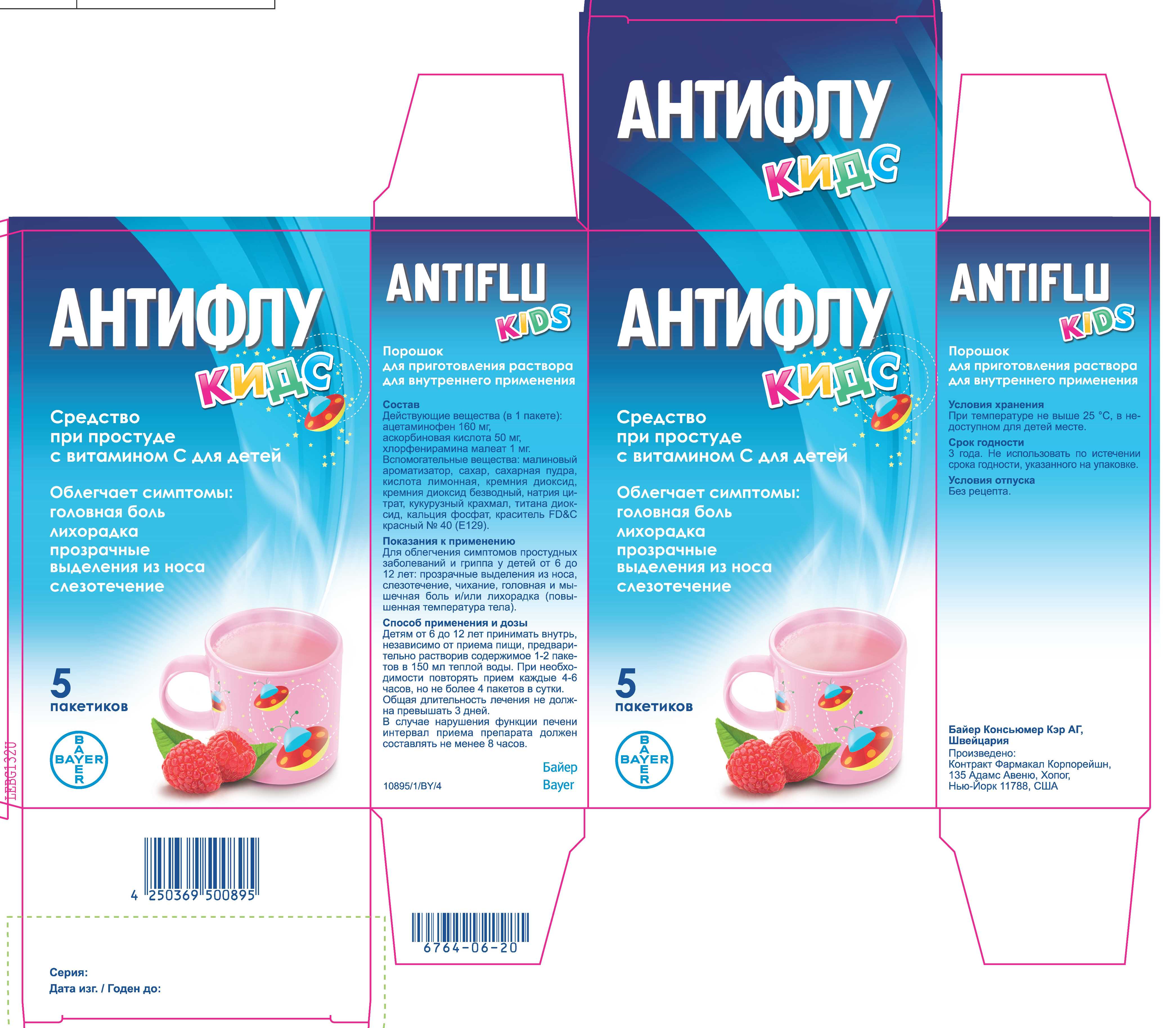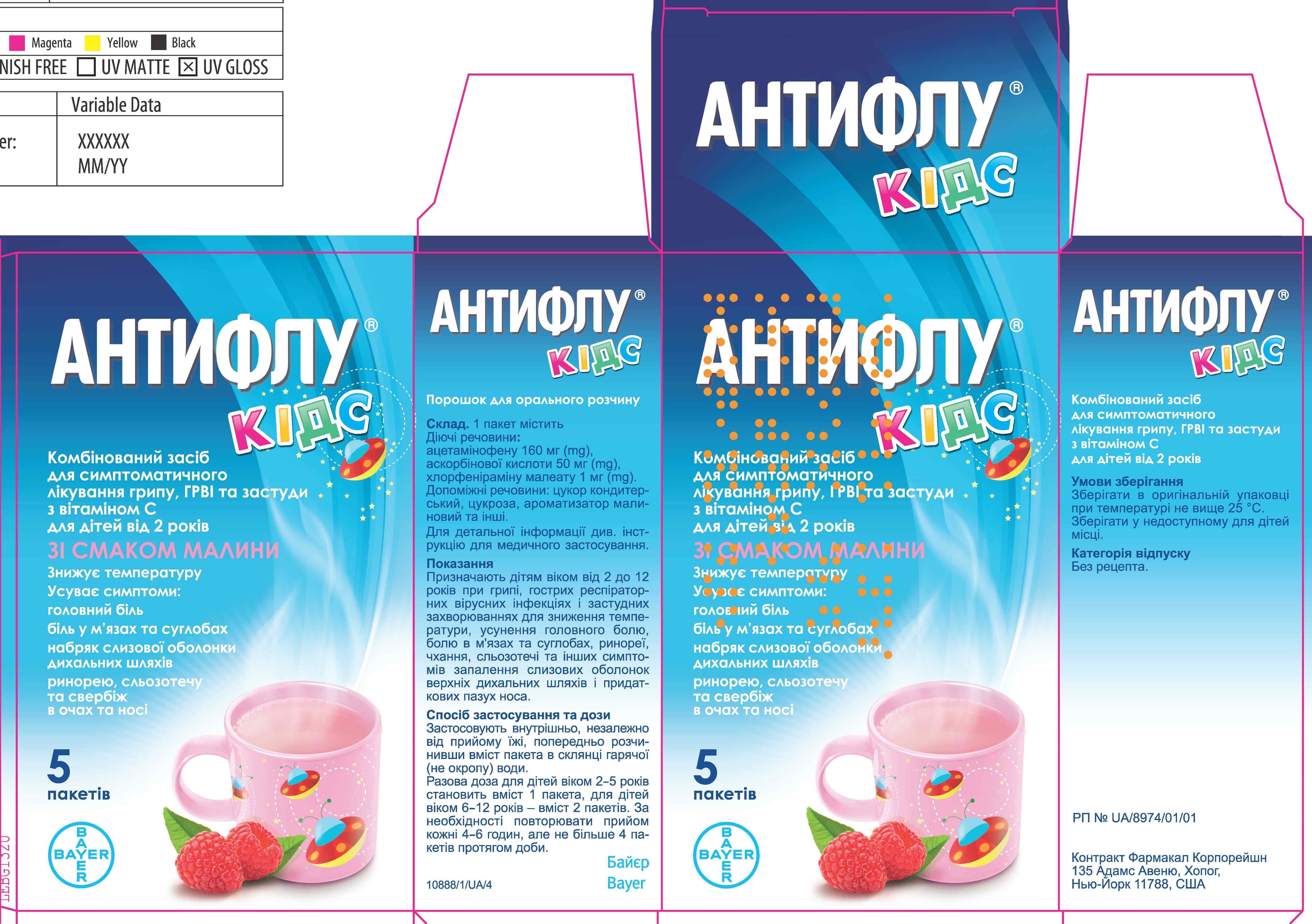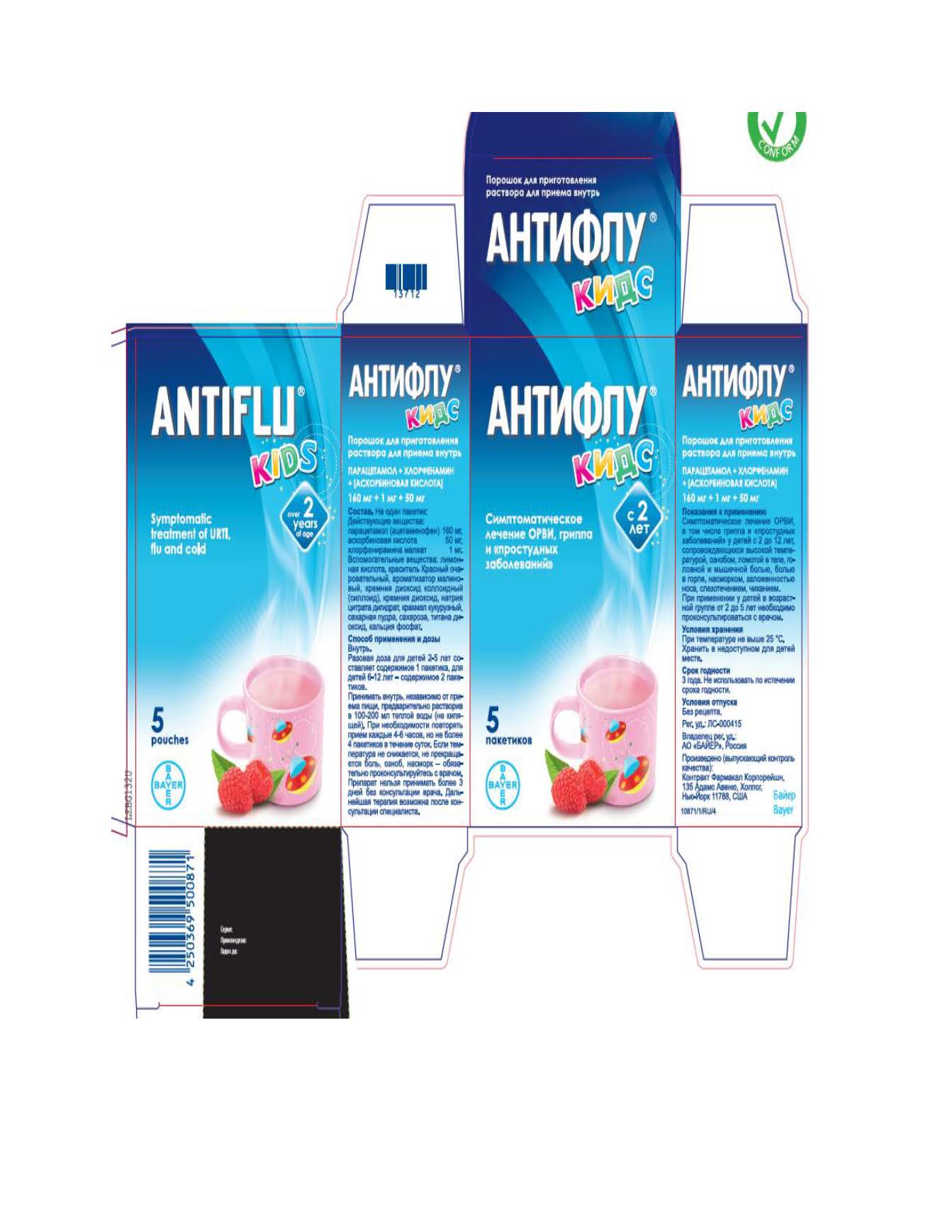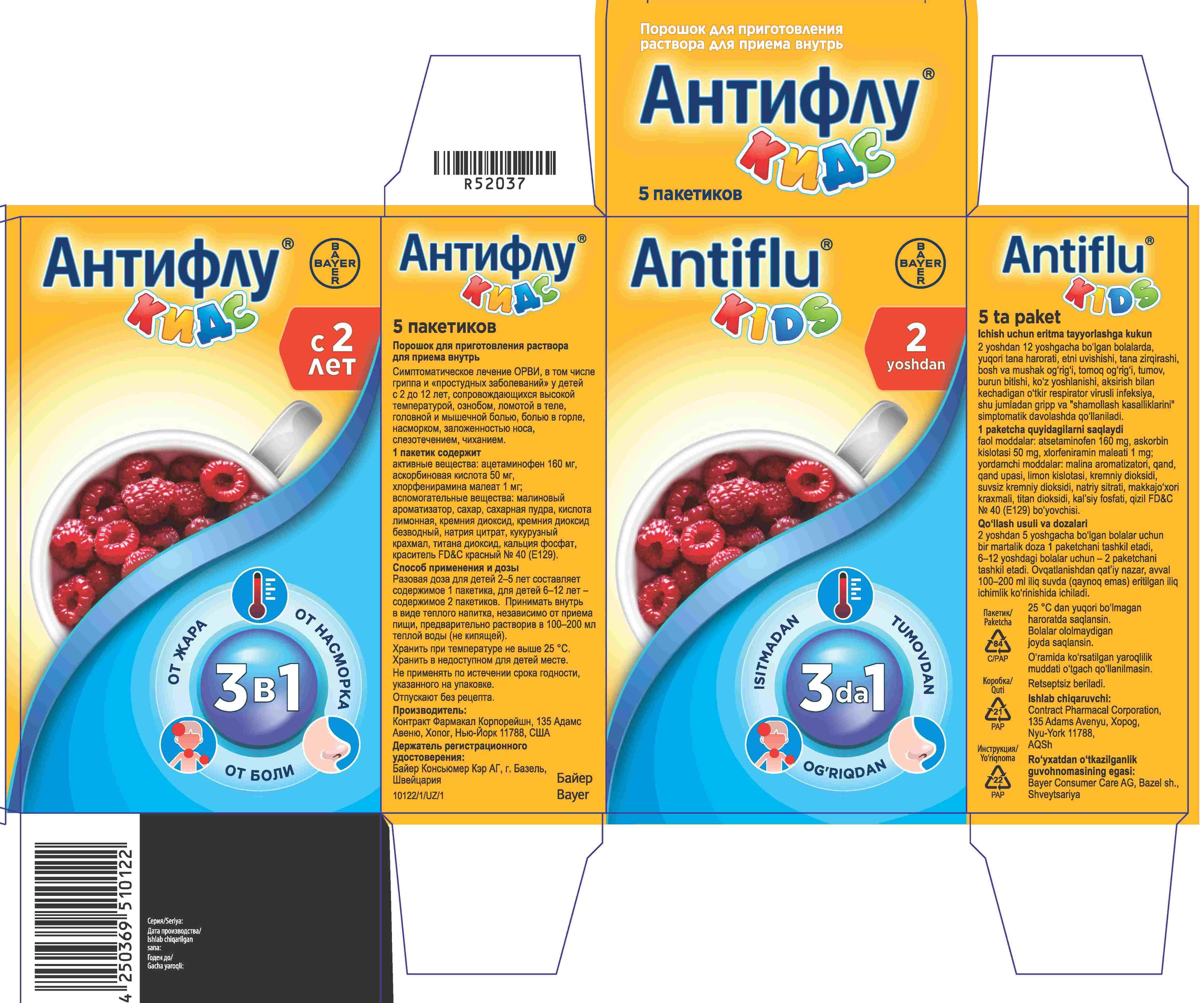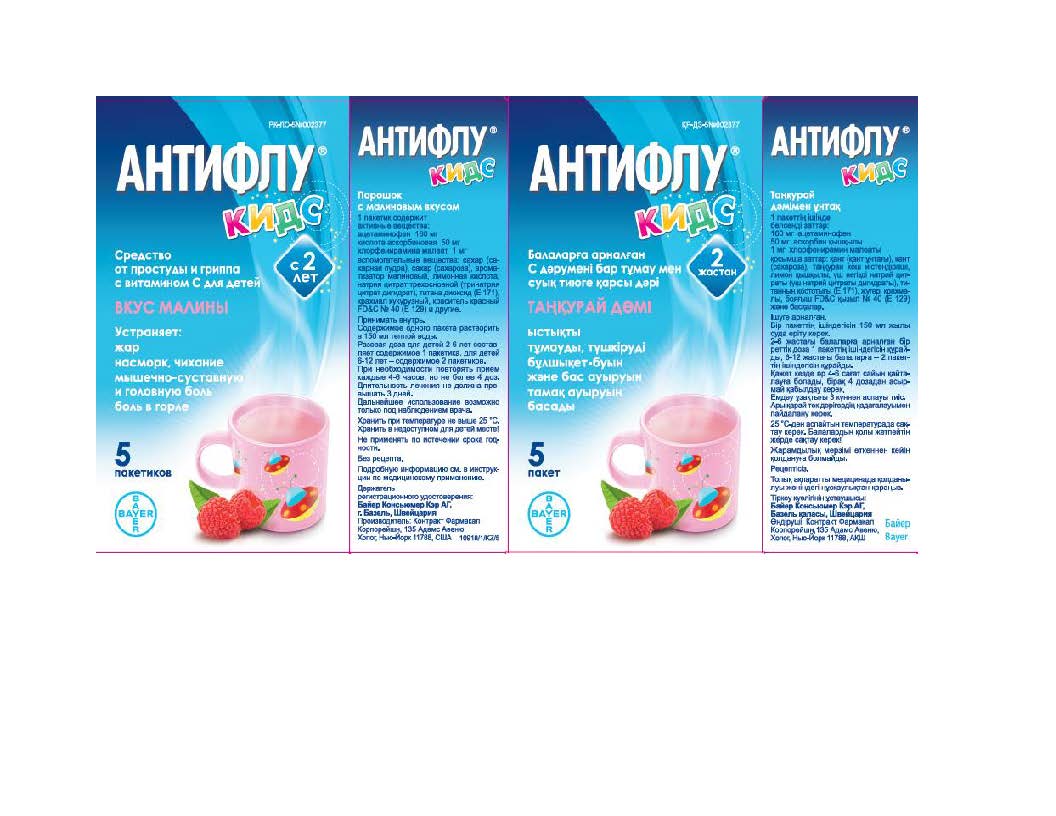 DRUG LABEL: Acetaminophen, Ascorbic acid, Chlorpheniramine Maleate
NDC: 10267-2949 | Form: POWDER, FOR SOLUTION
Manufacturer: Contract Pharmacal Corp.
Category: otc | Type: HUMAN OTC DRUG LABEL
Date: 20240508

ACTIVE INGREDIENTS: CHLORPHENIRAMINE MALEATE 1 mg/12000 mg; ASCORBIC ACID 50 mg/12000 mg; ACETAMINOPHEN 160 mg/12000 mg
INACTIVE INGREDIENTS: RASPBERRY; TRICALCIUM PHOSPHATE; FD&C RED NO. 40; SILICON DIOXIDE; STARCH, CORN; SUCROSE; TITANIUM DIOXIDE; ANHYDROUS CITRIC ACID; TRISODIUM CITRATE DIHYDRATE

2949K- Export